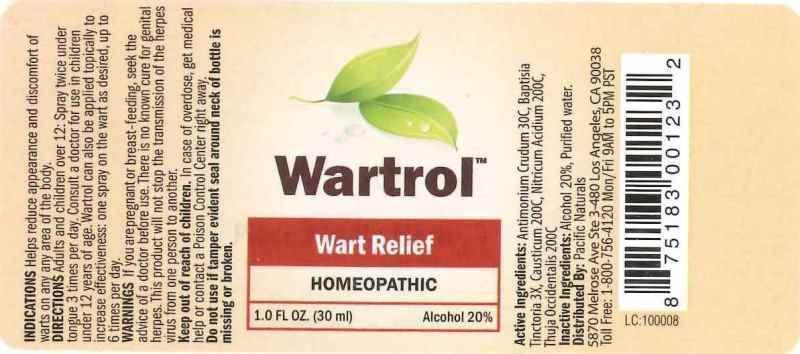 DRUG LABEL: WARTROL
NDC: 43695-0008 | Form: SPRAY
Manufacturer: Pacific Naturals
Category: homeopathic | Type: HUMAN OTC DRUG LABEL
Date: 20150109

ACTIVE INGREDIENTS: ANTIMONY TRISULFIDE 30 [hp_C]/1 mL; BAPTISIA TINCTORIA ROOT 3 [hp_X]/1 mL; CAUSTICUM 200 [hp_C]/1 mL; NITRIC ACID 200 [hp_C]/1 mL; THUJA OCCIDENTALIS LEAFY TWIG 200 [hp_C]/1 mL
INACTIVE INGREDIENTS: WATER; ALCOHOL

DRUG FACTS:

ACTIVE INGREDIENTS:

ANTIMONIOUM CRUDUM 30C, BAPTISIA TINCTORIA 3X, CAUSTICUM 200C, NITRICUM ACIDUM 200C, THUJA OCCIDENTALIS 200C

INDICATIONS:

Helps reduce appearance and discomfort of warts on any area of the body.

WARNINGS:

If you are pregnant or breast-feeding, seek the advice of a doctor before use.

There is no known cure for genital herpes. This product will not stop the transmission of the herpes virus from one person to another.

Keep out of reach of children. In case of overdose, get medical help or contact a Poison Control Center right away.

Do not use if tamper evident seal around neck of bottle is missing or broken.

Keep out of reach of children. In case of overdose, get medical help or contact a Poison Control Center right away.

DIRECTIONS:

Adults and children over 12: Spray twice under tongue three times per day. Consult a doctor for use in children under 12 years of age. Wartrol can also be applied topically to increase effectiveness: one spray on the wart as desired, up to 6 times per day.

INDICATIONS:

Helps reduce appearance and discomfort of warts on any area of the body.

INACTIVE INGREDIENTS:

Alcohol 20%, Purified water.

QUESTIONS:

Distributed By: Pacific Naturals

5870 Melrose Ave Ste 3-480 Los Angeles, CA 90038

1-800-756-4120 Mon/Fri 9AM to 5PM PST

PACKAGE LABEL DISPLAY:

Wartrol

Wart Relief

HOMEOPATHIC

1.0 FL OZ. (30 ml)